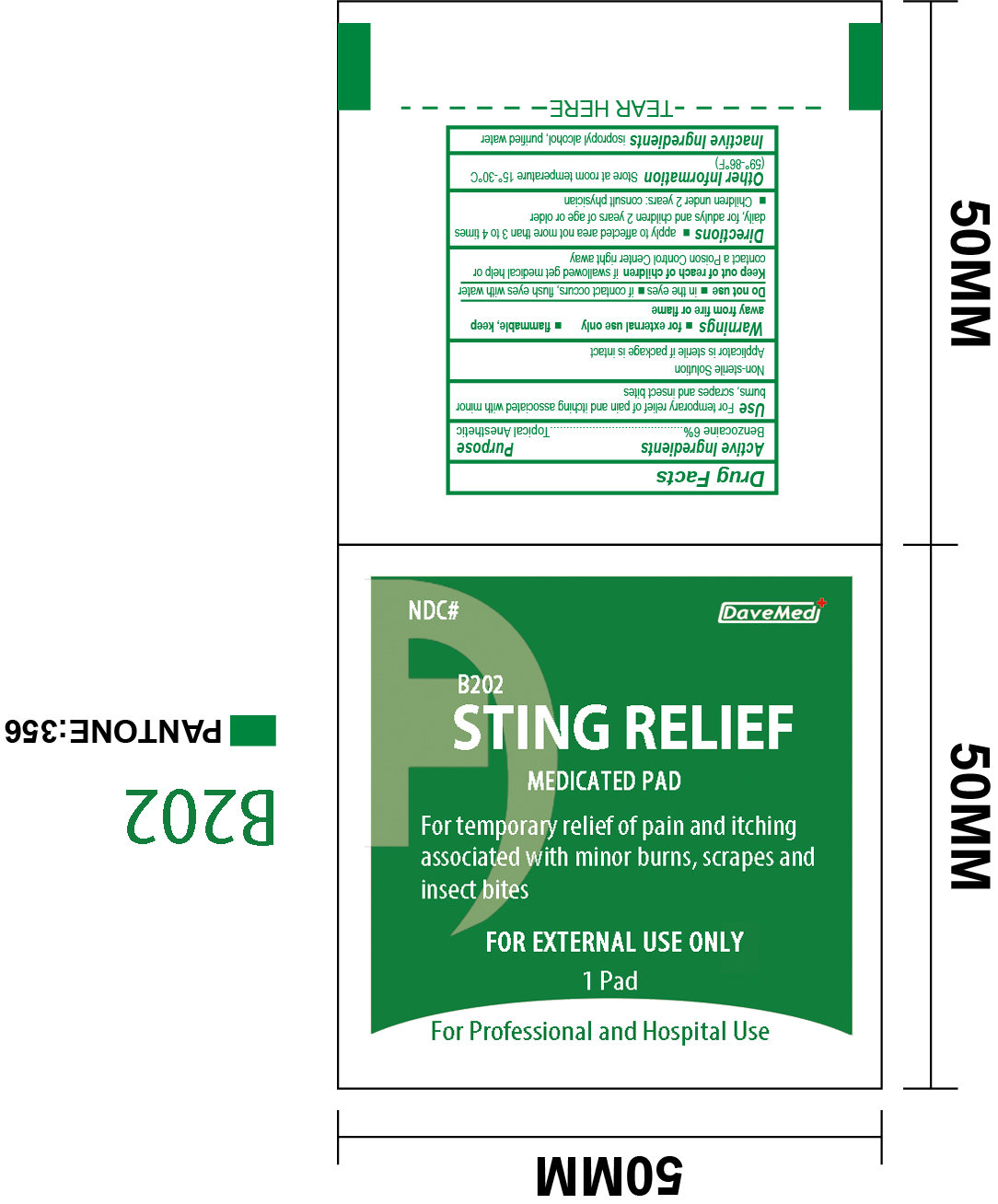 DRUG LABEL: Sting Relief Medicated Pad
NDC: 70897-004 | Form: SWAB
Manufacturer: Davemed Healthcare Co., Ltd
Category: otc | Type: HUMAN OTC DRUG LABEL
Date: 20190124

ACTIVE INGREDIENTS: BENZOCAINE 0.06 mg/1 1
INACTIVE INGREDIENTS: WATER; ISOPROPYL ALCOHOL

Sting relief medicated pad

Active Ingredients

Active ingredient

Benzocaine 6%

Purpose

Topical Anesthetic

Uses

First relief of pain and itching associated with minor burns, scrapes and insect bites

WARNINGS

- for external use only
- flammable, keep away from fire or flame

Do not use

- in the eyes
- if contact occurs, flush eyes with water

Keep out of reach of children. If swallowed get medical help or contact a Poison Control Center right away

Keep out of reach of children. If swallowed, get medical help or contact a Poison Control Center right away.

Directions

- apply to affected area not more than 3 to 4 times daily for adults and children 2 years of age or older.
- children under 2 years, consult physician

Inactive ingredients

isopropyl alcohol, purified water

Other Information

Store at room temperature 15o - 30oC (59o - 86oF)